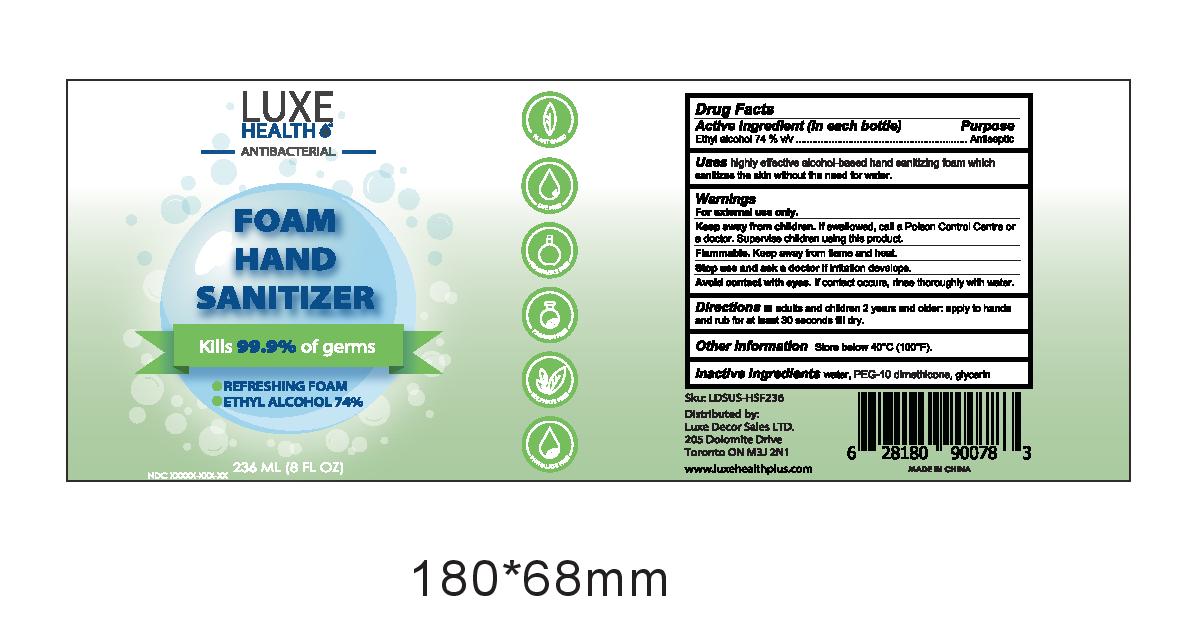 DRUG LABEL: Foam Hand Sanitizer
NDC: 80511-002 | Form: LIQUID
Manufacturer: Luxe Decore Sales Ltd.
Category: otc | Type: HUMAN OTC DRUG LABEL
Date: 20210129

ACTIVE INGREDIENTS: ALCOHOL 1480 mL/2000 mL
INACTIVE INGREDIENTS: GLYCERIN; WATER; PEG-10 DIMETHICONE (600 CST)

Luxe Decore Foaming Hand Sanitizer

Active Ingredient

Ethyl Alcohol 74% v/v

Purpose

Ethyl Alcohol 74% v/v................Antiseptic

Uses

highly effective alcohol-based hand sanitizing foam which sanitizes the skin without the need for water.

Warnings

For external use only.

KEEP OUT OF REACH OF CHILDREN

Keep away from children. If swallowed, call a Poison Control Centre or a doctor. Supervise children using this product.

WARNINGS

Flammable. Keep away from flame and heat.

Stop use and ask a doctor if irritation develops

WARNINGS

Avoid contact with eyes. If contact occurs, rinse thoroughly with water.

Directions

Directions ■ adults and children 2 years and older: apply to hands and rub for at least 30 seconds till dry

Other Information

Store below 40°C (100°F).

Inactive Ingredients

water, PEG-10 dimethicone, glycerin